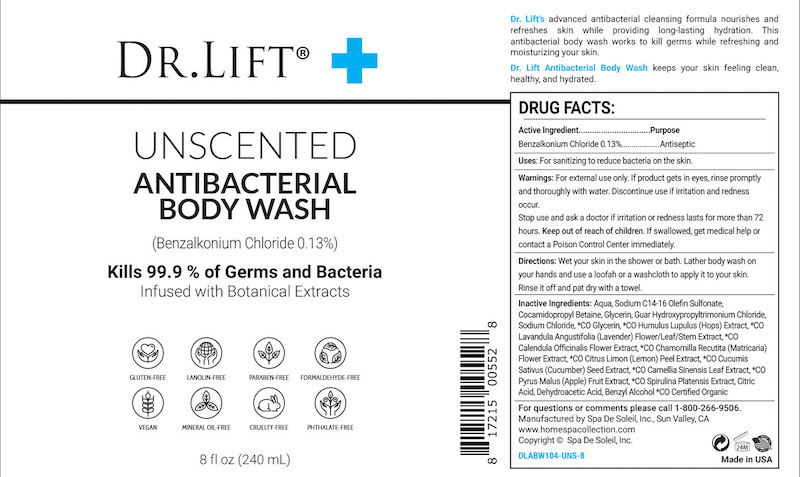 DRUG LABEL: Dr Lift Unscented Antibacterial Body Wash
NDC: 68062-2248 | Form: LIQUID
Manufacturer: Spa de Soleil
Category: otc | Type: HUMAN OTC DRUG LABEL
Date: 20260121

ACTIVE INGREDIENTS: BENZALKONIUM CHLORIDE 0.312 mg/240 mL
INACTIVE INGREDIENTS: COCAMIDOPROPYL BETAINE; SODIUM C14-16 OLEFIN SULFONATE; GLYCERIN; WATER

Dr Lift Unscented Antibacterial Body Wash

Active Ingredient

Benzalkonium Chloride 0.13%

Purpose

Antiseptic

Warnings

For external use only. If product gets in eyes, rinse promptly and thoroughly with water. Discontinue use if irritation and redness occur. Stop use and ask a doctor if irritation or redness lasts for more than 72 hours. Keep out of reach of children. If swallowed, get medical help or contact a Poison Control Center immediately.

Keep out of reach of children.

Directions

Directions: Wet your skin in the shower or bath. Lather body wash on your hands and use a loofah or a washcloth to apply it to your skin. Rinse it off and pat dry with a towel.

DOSAGE AND ADMINISTRATION

Place enough product in the palm of your hands to thoroughly cover you hands. Rub hands together briskly until product is completely absorbed and hands are dry.

Inactive Ingredients:

Inactive Ingredients

Aqua, Sodium C14-16 Olefin Sulfonate, Cocamidopropyl Betaine, Glycerin, Guar Hydroxypropyltrimonium Chloride, Sodium Chloride, *CO Glycerin, *CO Humulus Lupulus (Hops) Extract, *CO Lavandula Angustifolia (Lavender) Flower/Leaf/Stem Extract, *CO Calendula Officinalis Flower Extract, *CO Chamomilla Recutita (Matricaria) Flower Extract, *CO Citrus Limon (Lemon) Peel Extract, *CO Cucumis Sativus (Cucumber) Seed Extract, *CO Camellia Sinensis Leaf Extract, *CO Pyrus Malus (Apple) Fruit Extract, *CO Spirulina Platensis Extract, Citric Acid, Dehydroacetic Acid, Benzyl Alcohol.

*CO Certified Organic